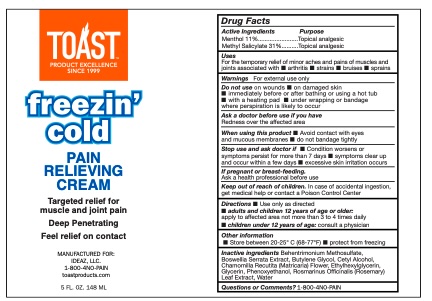 DRUG LABEL: Toast Freezin Cold
NDC: 78983-104 | Form: CREAM
Manufacturer: IDEAZ, LLC
Category: otc | Type: HUMAN OTC DRUG LABEL
Date: 20250616

ACTIVE INGREDIENTS: MENTHOL 11 g/100 g; METHYL SALICYLATE 31 g/100 g
INACTIVE INGREDIENTS: BOSWELLIA SERRATA OIL; GLYCERIN; ROSMARINUS OFFICINALIS (ROSEMARY) LEAF OIL; PHENOXYETHANOL; WATER; ETHYLHEXYLGLYCERIN; CETYL ALCOHOL; MATRICARIA CHAMOMILLA FLOWERING TOP OIL; 1,4-BUTANEDIOL

Toast Freezin' Cold - 78983-104

Active Ingredient

Menthol 11%

Methyl Salicylate 31%

Purpose

Topical analgesic

Uses

for the temporary relief of minor aches and pains of

muscles and joints associated with ■ arthritis ■ strains

■ bruises ■ sprains

Warnings

For external use only

Do not use

on wounds ■ on damaged skin

■ immediately before or after bathing or using a hot tub

■ with a heating pad ■ under wrapping or bandage

where perspiration is likely to occur

When using this product

■ Avoid contact with eyes

and mucous membranes ■ do not bandage tightly

Stop using consult a doctor if

■ Condition worsens or

symptoms persist for more than 7 days ■ symptoms clear up

and occur within a few days ■ excessive skin irritation occurs

Keep out of reach of children

In case of accidental ingestion, get medical help or contact a Poison Control Center

If pregnant or breast-feeding

ask a healthcare professional before use.

Directions

■ Use only as directed

■ adults and children 12 years of age or older:

apply to affected area not more than 3 to 4 times daily

■ children under 12 years of age: consult a physician

Other information

■ Store between 20-25° C (68-77°F) ■ protect from freezing

Inactive ingredients

Behentrimonium Methosulfate, Boswellia Serrata Extract, Butylene Glycol, Cetyl Alcohol, Chamomilla Recutita (Matricaria) Flower, Ethylhexylglycerin, Glycerin, Phenoxyethanol, Rosmarinus Officinalis (Rosemary) Leaf Extract, Water

Questions or Comments?

1-800-4NO-PAIN